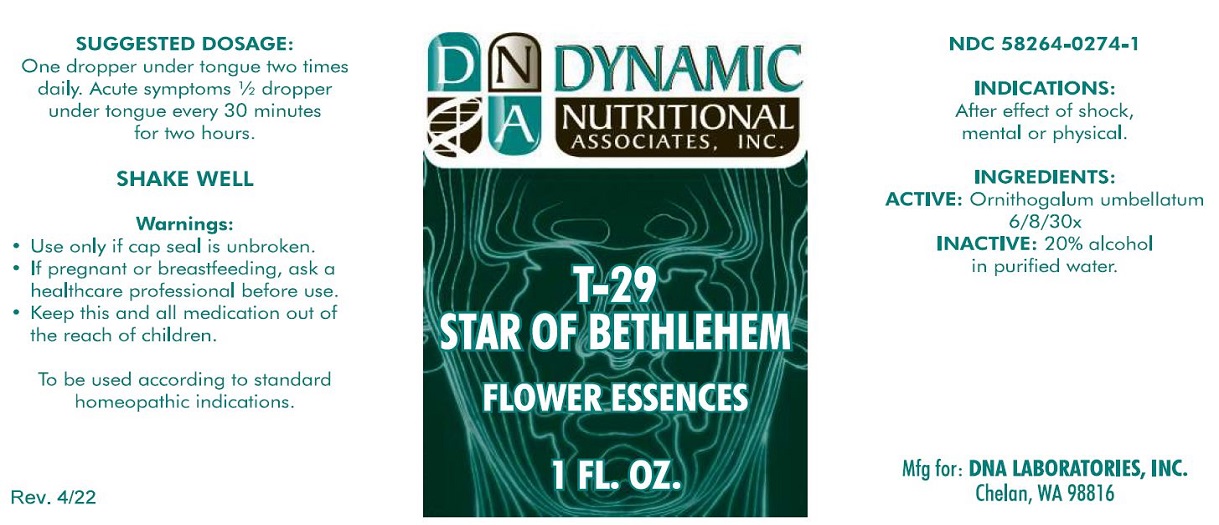 DRUG LABEL: T-29
NDC: 58264-0274 | Form: SOLUTION
Manufacturer: DNA Labs, Inc.
Category: homeopathic | Type: HUMAN OTC DRUG LABEL
Date: 20250109

ACTIVE INGREDIENTS: ORNITHOGALUM UMBELLATUM 30 [hp_X]/1 mL
INACTIVE INGREDIENTS: ALCOHOL; WATER

T-29

NDC 58264-0274-1

INDICATIONS AND USAGE

INDICATIONS

After effect of shock, mental or physical.

ACTIVE INGREDIENT

INGREDIENTS

Ornithogalum umbellatum 6/8/30x, 20% alcohol in purified water.

SUGGESTED DOSAGE

One dropper under tongue two times daily. Acute symptoms ½ dropper under tongue every 30 minutes for two hours.

STORAGE AND HANDLING

SHAKE WELL

Warnings

- Use only if cap seal is unbroken.

PREGNANCY OR BREAST FEEDING

- As with drugs if you are pregnant or nursing a baby seek professional advice before using this product.

KEEP OUT OF REACH OF CHILDREN

- Keep this and all medication out of the reach of children.

To be used according to standard homeopathic indications.

PRINCIPAL DISPLAY PANEL - 1 FL. OZ. Bottle Label

DYNAMIC
NUTRITIONAL
ASSOCIATES, INC.

T-29
STAR OF BETHLEHEM

FLOWER ESSENCES

1 FL. OZ.